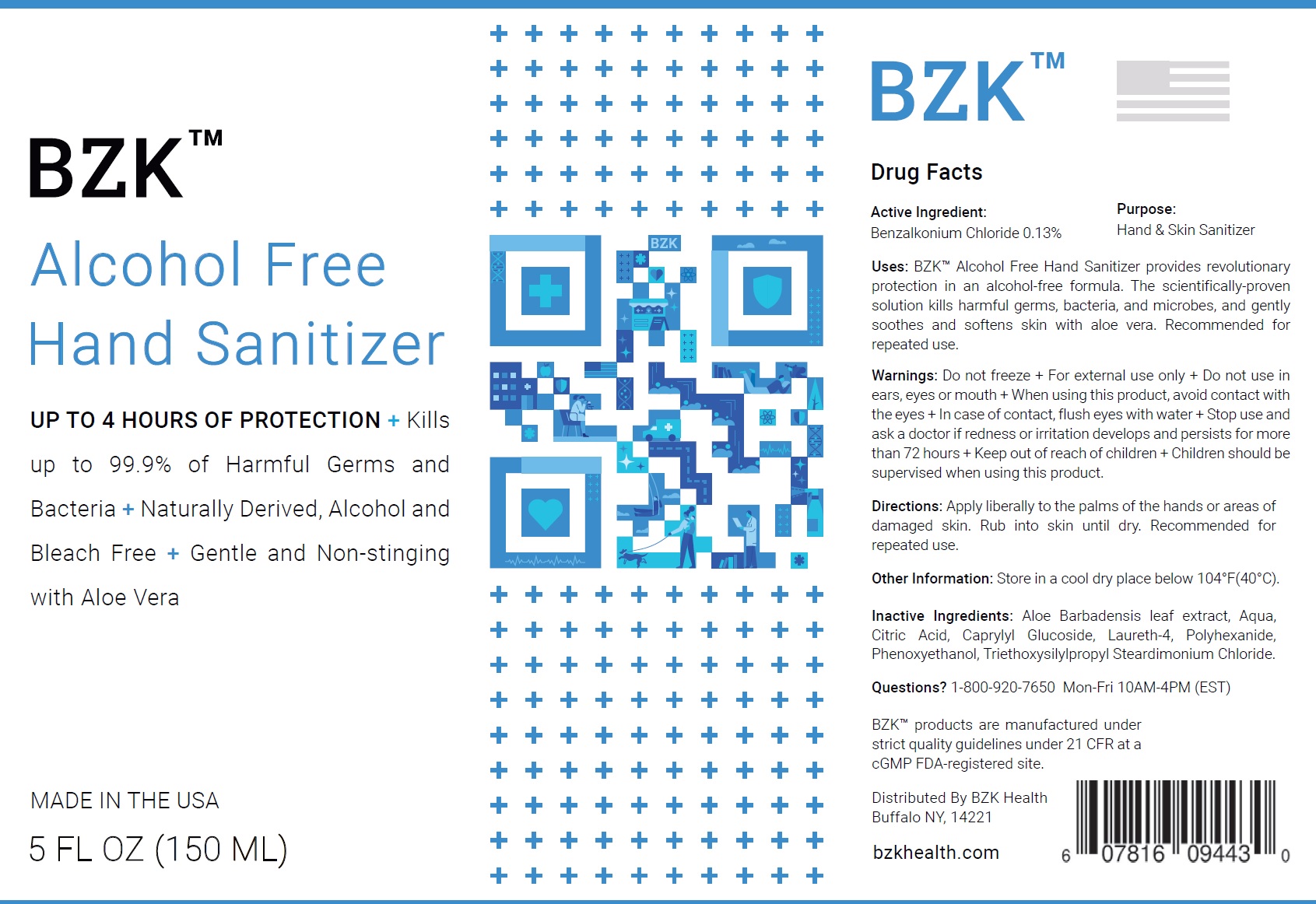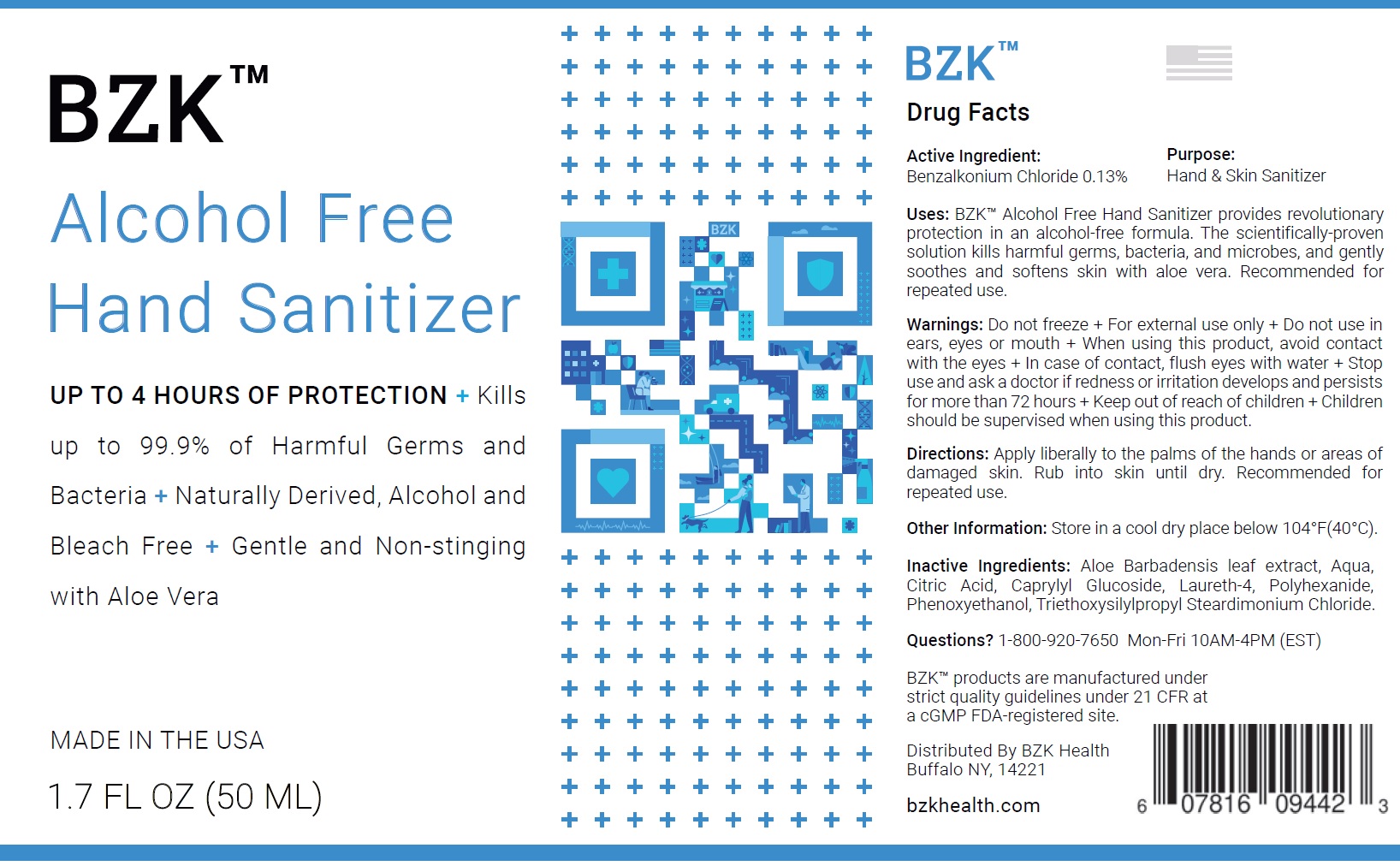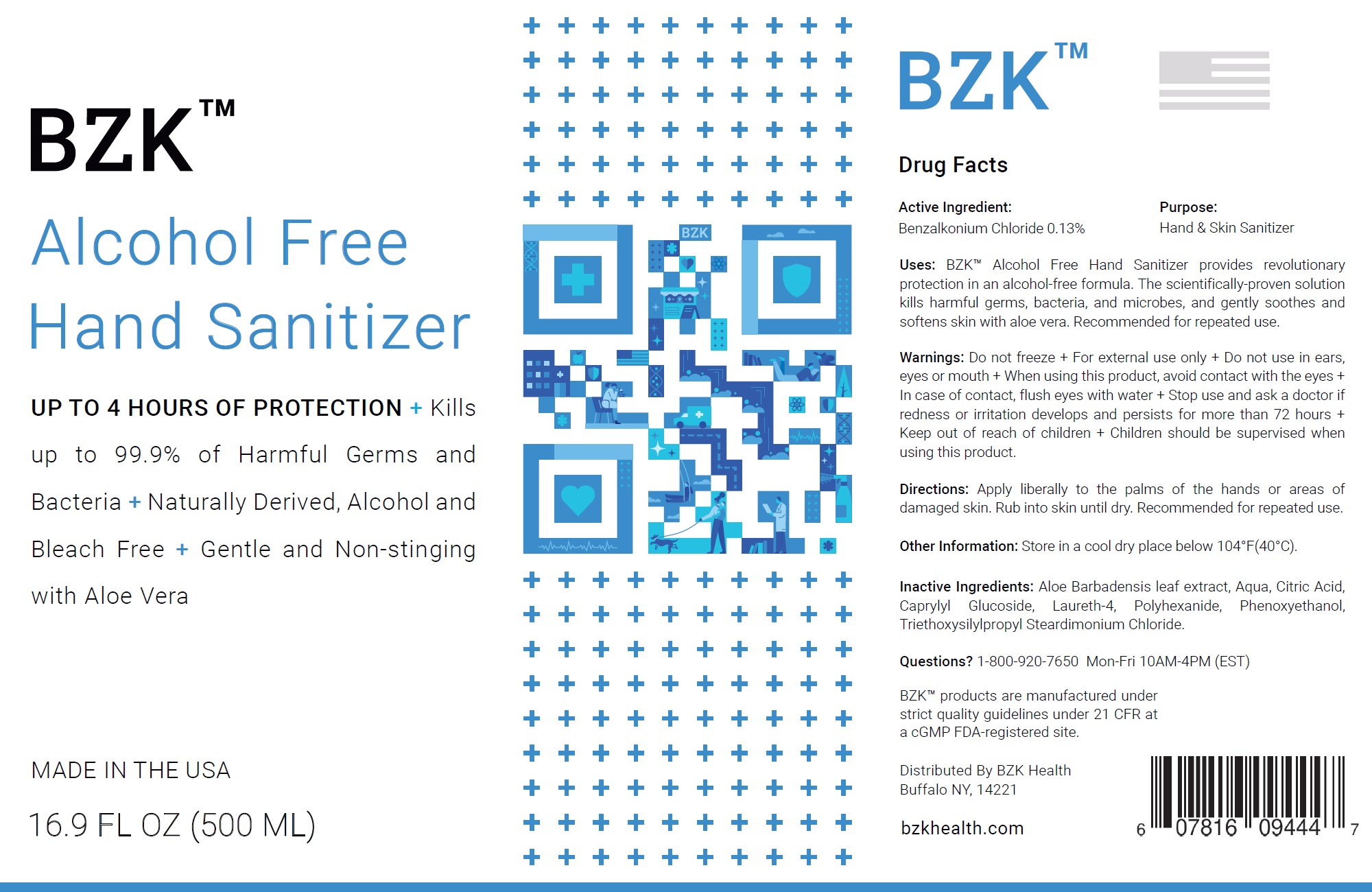 DRUG LABEL: BZK Alcohol Free Hand Sanitizer
NDC: 81529-002 | Form: LIQUID
Manufacturer: Premium PPE, LLC
Category: otc | Type: HUMAN OTC DRUG LABEL
Date: 20210308

ACTIVE INGREDIENTS: BENZALKONIUM CHLORIDE 1.3 mg/1 mL
INACTIVE INGREDIENTS: ALOE VERA LEAF; WATER; CITRIC ACID MONOHYDRATE; CAPRYLYL GLUCOSIDE; LAURETH-4; POLIHEXANIDE; PHENOXYETHANOL; TRIETHOXYSILYLPROPYL STEARDIMONIUM CHLORIDE

BZK Alcohol Free Hand Sanitizer

Active Ingredient:

Benzalkonium Chloride 0.13%

Purpose:

Hand & Skin Sanitizer

Uses:

BZK™ Alcohol Free Hand Sanitizer provides revolutionary protection in an alcohol-free formula. The scientifically-proven solution kills harmful germs, bacteria, and microbes, and gently soothes and softens skin with aloe vera. Recommended for repeated use.

Warnings:

Do not freeze

+ For external use only

Do not use

+ in ears, eyes or mouth

When using this product,

+avoid contact with the eyes

+ In case of contact, flush eyes with water

Stop use and ask a doctor if

+redness or irritation develops and persists for more than 72 hours

Keep out of reach of children

+Children should be supervised when using this product.

Directions:

Apply liberally to the palms of the hands or areas of damaged skin. Rub into skin until dry. Recommended for repeated use.

Other Information:

Store in a cool dry place below 104°F(40°C).

Inactive Ingredients:

Aloe Barbadensis leaf extract, Aqua, Citric Acid, Caprylyl Glucoside, Laureth-4, Polyhexanide, Phenoxyethanol, Triethoxysilylpropyl Steardimonium Chloride.

Questions?

1-800-920-7650 Mon-Fri 10AM-4PM (EST)